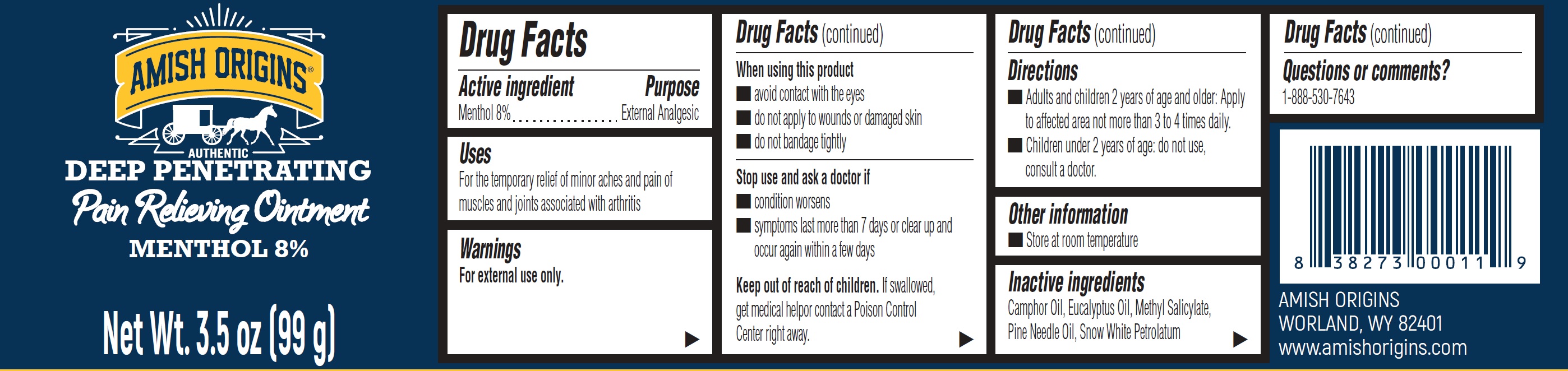 DRUG LABEL: Amish Origins Pain Relieving Menthol 8%
NDC: 62212-002 | Form: OINTMENT
Manufacturer: Amish Origins Management, LLC
Category: otc | Type: HUMAN OTC DRUG LABEL
Date: 20240229

ACTIVE INGREDIENTS: MENTHOL 80 mg/1 g
INACTIVE INGREDIENTS: CAMPHOR OIL; EUCALYPTUS OIL; METHYL SALICYLATE; PINE NEEDLE OIL (PINUS SYLVESTRIS)

Amish Origins Pain Relieving Ointment, Menthol 8%

Active ingredient

Menthol 8%

Purpose

External Analgesic

Uses

For the temporary relief of minor aches and pain of muscles and joints associated with arthritis

Warnings

For external use only.

When using this product

- avoid contact with the eyes
- do not apply to wounds or damaged skin
- do not bandage tightly

Stop use and ask a doctor if

- condition worsens
- symptoms last more than 7 days or clear up and occur again within a few days

Keep out of reach of children.

If swallowed, get medical helpor contact a Poison Control Center right away.

Directions

- Adults and children 2 years of age and older: Apply to affected area not more than 3 to 4 times daily.
- Children under 2 years of age: do not use, consult a doctor.

Other information

- Store at room temperature

Inactive ingredients

Camphor Oil, Eucalyptus Oil, Methyl Salicylate, Pine Needle Oil, Snow White Petrolatum

Questions or comments?

1-888-530-7643